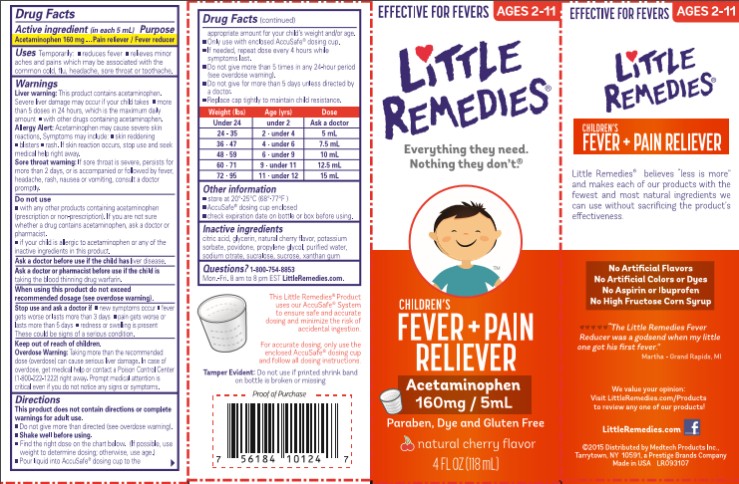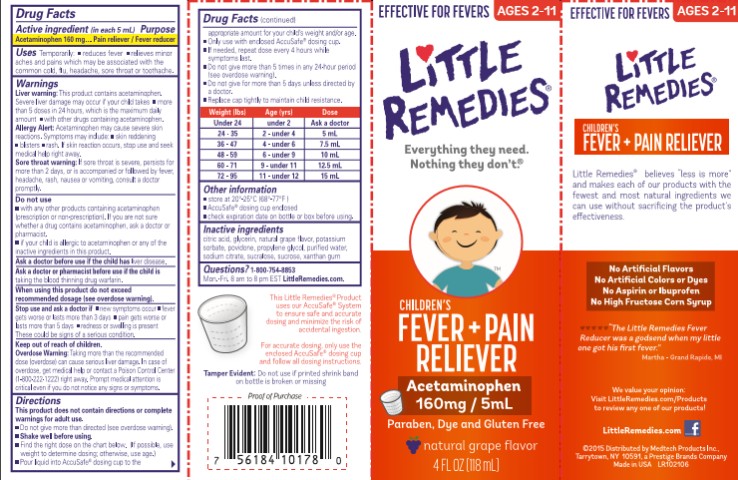 DRUG LABEL: Little Remedies Childrens Fever Pain Reliever
NDC: 63029-602 | Form: LIQUID
Manufacturer: Medtech Products Inc.
Category: otc | Type: HUMAN OTC DRUG LABEL
Date: 20250117

ACTIVE INGREDIENTS: ACETAMINOPHEN 160 mg/5 mL
INACTIVE INGREDIENTS: CITRIC ACID MONOHYDRATE; GLYCERIN; PROPYLENE GLYCOL; POLYETHYLENE GLYCOL, UNSPECIFIED; WATER; SUCRALOSE; XANTHAN GUM; HIGH FRUCTOSE CORN SYRUP; SODIUM BENZOATE

Little Remedies Childrens Fever Pain Reliever

Drug Facts

Active Ingredient

(in each 5 mL teaspoon)
Acetaminophen 160mg

Purpose

Pain Reliever/Fever Reducer

Uses

Temporarily:

- reduces fever
- relieves minor aches and pains which may be associated with the common cold, flu, headache, sore throat or toothache.

Warnings

Liver warning: This product contains acetaminophen. Severe liver damage may occur if your child takes

- more than 5 doses in 24 hours, which is the maximum daily amount
- with other drugs containing acetaminophen.

Ask a doctor before use

if your child has liver disease.

Ask a doctor or pharmacist before use

if your child is taking the blood thinning drug warfarin.

Do not use:

- with any other products containing acetaminophen, (prescription or non-prescription). If you are not sure whether a drug contains acetaminophen, ask a doctor or pharmacist.
- if your child is allergic to acetaminophen or any of the inactive ingredients in this product.

Sore Throat Warning: if sore throat is severe, persists for more than 2 days, or is accompanied or followed by fever, headache, rash, nausea, or vomiting, consult a doctor promptly.

When using this product,

DO NOT EXCEED RECOMMENDED DOSAGE: taking more than the recommended dose (overdose) may not provide more relief and may cause liver damage.

Stop use and ask a doctor if:

- new symptoms occur
- fever gets worse or lasts more than 3 days
- pain gets worse or lasts more than 5 days
- redness or swelling is present. These could be signs of a serious condition.

Overdose Warning:

Taking more than the recommended dose (overdose) can cause serious liver damage. In case of overdose, get medical help or contact a Poison Control Center right away (1-800-222-1222). Prompt medical attention is critical even if you do not notice any signs of symptoms.

Directions

This product does not contain directions or complete warnings for adult use.

- Do not give more than directed (see overdose warning).
- Shake well before using.
- Find the right dose on the chart below. (If possible, use weight to determine dosing; otherwise, use age.)
- Invert bottle and gently squeeze liquid into AccuSafeTM dosing cup to the appropriate amount for your child’s weight and/or age.
- Only use with enclosed AccuSafeTM dosing cup.
- If needed, repeat dose every 4 hours while symptoms last.
- Do not give more than 5 days in any 24-hour period (see overdose warning).
- Do not give more than 5 days unless directed by a doctor.
- Replace cap tightly to maintain child resistance.

Weight (lb) | Age (yr) | Dose
Under 24 | Under 2 | Ask a doctor
24-35 | 2 – Under 4 | 1 tsp or 5mL
36-47 | 4 – Under 6 | 1 ½ tsp or 7.5mL
48-59 | 6 – under 9 | 2 tsp or 10 mL
60-71 | 9 – under 11 | 2 ½ tsp or 12.5mL
72-95 | 11 – under 12 | 3 tsp or 15mL

Other Information

- Store at 20-25ºC (68-77ºF)
- AccuSafeTM Dosing cup enclosed.
- Tamper Evident: DO NOT USE if printed skrink band on bottle is broken or missing.
- Check expiration date on bottle or box before using.

Inactive Ingredients:

Citric Acid, Glycerin, High Fructose Corn Syrup, Natural Flavors, Polyethylene Glycol, Propylene Glycol, Purified Water, Sodium Benzoate, Sucralose, Xanthan Gum

Questions?

For further information you may contact us at: 1-800-7-LITTLE Mon. – Fri. 8:00 a.m. to 8:00 p.m. EST, or visit us at www.LittleRemedies.com.

PRINCIPAL DISPLAY PANEL

Little Remedies®
CHILDREN’S FEVER + PAIN RELIEVER
Acetaminophen
NATURAL CHERRY FLAVOR
4 FL OZ (118 mL)

PRINCIPAL DISPLAY PANEL

Little Remedies®
CHILDREN’S FEVER + PAIN RELIEVER
Acetaminophen
NATURAL GRAPE FLAVOR
4 FL OZ (118 mL)